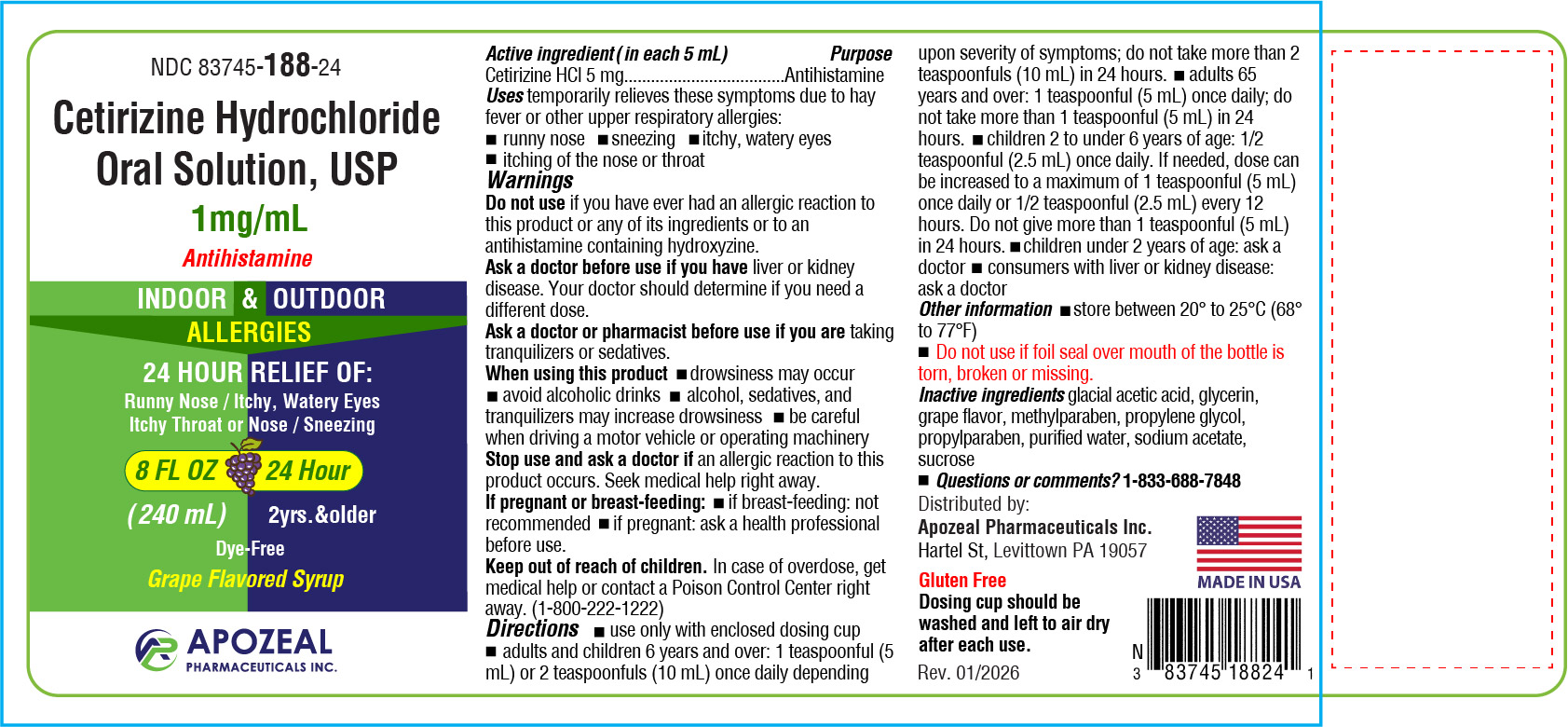 DRUG LABEL: Cetrizine Hydrochloride
NDC: 83745-188 | Form: SOLUTION
Manufacturer: APOZEAL PHARMACEUTICALS INC
Category: otc | Type: HUMAN OTC DRUG LABEL
Date: 20260131

ACTIVE INGREDIENTS: CETIRIZINE HYDROCHLORIDE 1 mg/1 mL
INACTIVE INGREDIENTS: METHYLPARABEN; PROPYLPARABEN; GLYCERIN; PROPYLENE GLYCOL; SODIUM ACETATE; GRAPE; ACETIC ACID; SUCROSE; WATER

Cetirizine Hydrochloride Oral Solution 1 mg/mL

Drug Facts

Active ingredient (in each 5 mL teaspoonful) Purpose

Cetirizine HCl 5 mg----------------------------------Antihistamine

Purpose

Antihistamine

Uses

temporarily relieves these symptoms due to hay fever or upper respiratory allergies:

- runny nose
- sneezing
- itchy, watery eyes
- itching of the nose or throat

Warnings

Do not use if you have ever had an allergic reaction to this product or any of its ingredients or to an antihistamine containing hydroxyzine.

Ask a doctor before use if you have liver or kidney disease. Your doctor should determine if you need a different dose.

Ask a doctor or pharmacist before use if you are taking tranquilizers or sedatives.

When using this product

- drowsiness may occur
- avoid alcoholic drinks
- alcohol, sedatives, and tranquilizers may increase drowsiness
- be careful when driving a motor vehicle or operating machinery

Stop use and ask a doctor if an allergic reaction to this product occurs. Seek medical help right away.

If pregnant or breast-feeding:

- if breast-feeding: not recommended
- if pregnant: ask a health professional before use.

Keep out of reach of children. In case of overdose, get medical help or contact a Poison Control Center right away. (1-800-222-1222)

Directions

- use only with enclosed dosing cup
- adults and children 6 years and over: 1 teaspoonful (5 mL) or 2 teaspoonfuls (10 mL) once daily depending upon severity of symptoms; do not take more than 2 teaspoonfuls (10 mL) in 24 hours.
- adults 65 years and over: 1 teaspoonful (5 mL) once daily; do not take more than 1 teaspoonful (5 mL) in 24 hours.
- children 2 to under 6 years of age: 1/2 teaspoonful (2.5 mL) once daily. If needed, dose can be increased to a maximum of 1 teaspoonful (5 mL) once daily or 1/2 teaspoonful (2.5 mL) every 12 hours. Do not give more than 1 teaspoonful (5 mL) in 24 hours.
- children under 2 years of age: ask a doctor
- consumers with liver or kidney disease: ask a doctor

Other information

- store between 20° to 25°C (68° to 77°F)
- Do not use if foil seal over mouth of the bottle is torn, broken or missing.
- Gluten Free
- Dosing cup should be washed and left to air dry after each use.

Inactive ingredients

glacial acetic acid, glycerine, grape flavor, methylparaben, propylene glycol, propylparaben, purified water, sodium acetate, sucrose

Questions or comments?

1-833-688-7848

Distributed by:
Apozeal Pharmaceuticals Inc.
Hartel St, Levittown PA 19057

PRINCIPAL DISPLAY PANEL

NDC 83745-188-24

Cetirizine Hydrochloride

Oral Solution 1 mg/mL
Antihistamine

INDOOR & OUTDOOR
ALLERGIES

(240 mL)

Grape Flavored Syrup